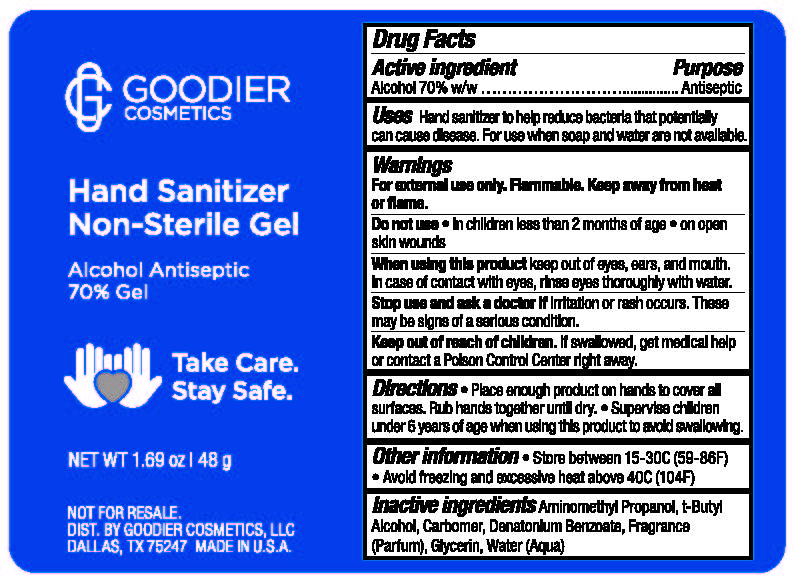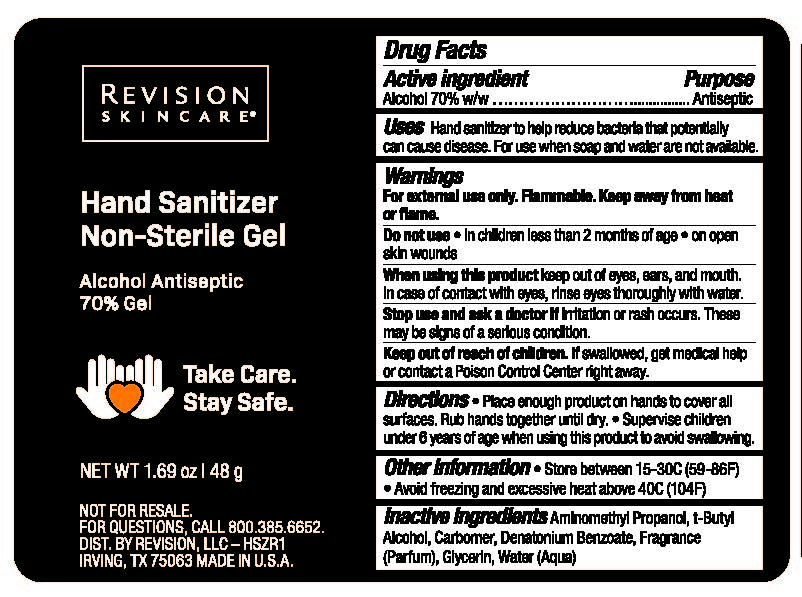 DRUG LABEL: Hand Sanitizer
NDC: 10477-2630 | Form: GEL
Manufacturer: Goodier Cosmetics
Category: otc | Type: HUMAN OTC DRUG LABEL
Date: 20221221

ACTIVE INGREDIENTS: ALCOHOL 73 mL/100 mL
INACTIVE INGREDIENTS: AMINOMETHYLPROPANOL 0.1 mL/100 mL; TERT-BUTYL ALCOHOL 0.09 mL/100 mL; CARBOXYPOLYMETHYLENE 0.3 mL/100 mL; DENATONIUM BENZOATE 0.0004 mL/100 mL; GLYCERIN 3.4 mL/100 mL; WATER 18.8 mL/100 mL

Hand Sanitizer

Active ingredient Alcohol 70% w/w

Purpose Antiseptic

INDICATIONS AND USAGE

Uses Hand sanitizer to help reduce bacteria that potentially can cause disease. For use when soap and water are not available.

Warnings

For external use only. Flammable. Keep away from heat or flame.

Do not use • in children less than 2 months of age • on open skin wounds

When using this product keep out of eyes, ears, and mouth. In case of contact with eyes, rinse eyes thoroughly with water.

Stop use and ask a doctor if irritation or rash occurs. These may be signs of a serious condition.

Keep out of reach of children. If swallowed, get medical help or contact a Poison Control Center right away.

DOSAGE AND ADMINISTRATION

Directions • Place enough product on hands to cover all surfaces. Rub hands together until dry. • Supervise children under 6 years of age when using this product to avoid swallowing.

Other information • Store between 15-30C (59-86F) • Avoid freezing and excessive heat above 40C (104F)

INACTIVE INGREDIENT

Inactive ingredients Aminomethyl Propanol, t-Butyl Alcohol, Carbomer, Denatonium Benzoate, Fragrance (Parfum), Glycerin, Water (Aqua)

Revision Hand Sanitizer Label

Goodier Hand Sanitizer Label